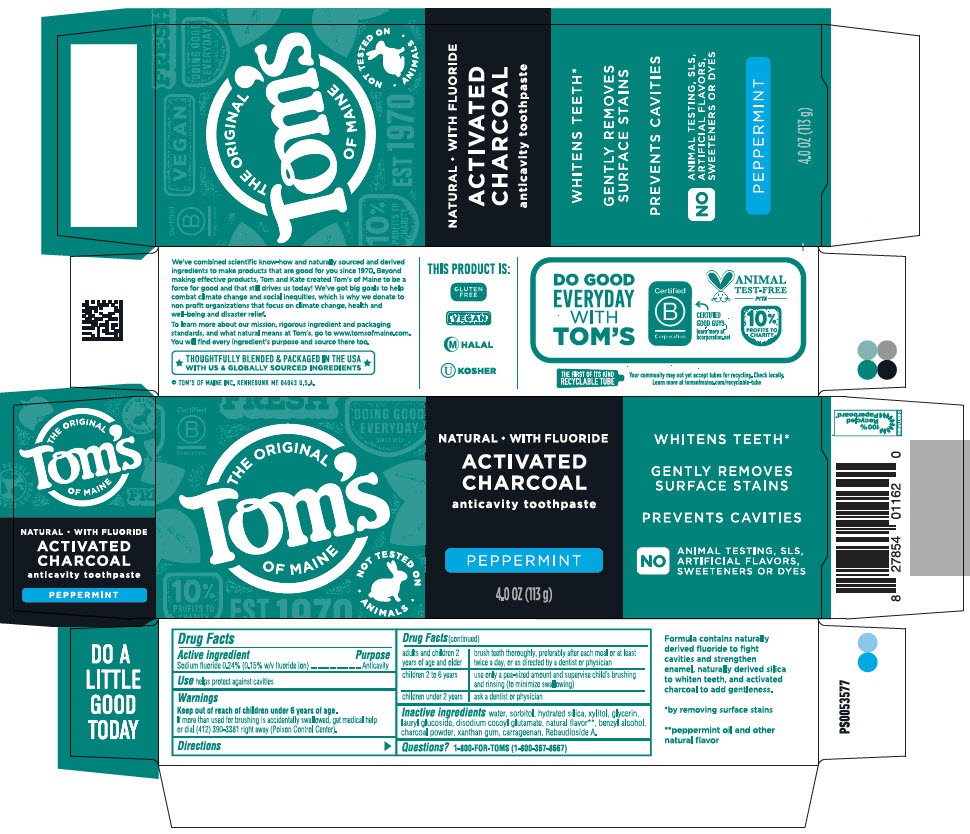 DRUG LABEL: Peppermint Charcoal Anticavity PCFT6
NDC: 51009-900 | Form: PASTE, DENTIFRICE
Manufacturer: Tom's of Maine, Inc.
Category: otc | Type: HUMAN OTC DRUG LABEL
Date: 20260212

ACTIVE INGREDIENTS: SODIUM FLUORIDE 0.0024 g/1 g
INACTIVE INGREDIENTS: HYDRATED SILICA; WATER; SORBITOL; GLYCERIN; XYLITOL; LAURYL GLUCOSIDE; SODIUM COCOYL GLUTAMATE; BENZYL ALCOHOL; ACTIVATED CHARCOAL; XANTHAN GUM; CARRAGEENAN; REBAUDIOSIDE A

Peppermint Charcoal Anticavity PCFT6
gently whitens teeth / fights cavities / safe for enamel / safe for everyday use

Drug Facts

Active ingredient

Sodium fluoride 0.24% (0.15% w/v fluoride ion)

Purpose

Anticavity

Use

helps protect against cavities

Warnings

Keep out of reach of children under 6 years of age.

If more than used for brushing is accidentally swallowed, get medical help or dial (412) 390-3381 right away (Poison Control Center).

Directions

adults and children 2 years of age and older | brush teeth thoroughly, preferably after each meal or at least twice a day, or as directed by a dentist or physician
children 2 to 6 years | use only a pea-sized amount and supervise child's brushing and rinsing (to minimize swallowing)
children under 2 years | ask a dentist or physician

Inactive ingredients

water, sorbitol, hydrated silica, xylitol, glycerin, lauryl glucoside, disodium cocoyl glutamate, natural flavor [peppermint oil and other natural flavor] , benzyl alcohol, charcoal powder, xanthan gum, carrageenan, Rebaudioside A.

Questions?

1-800-FOR-TOMS (1-800-367-8667)

PRINCIPAL DISPLAY PANEL - 113 g Tube Carton

THE ORIGINAL
Tom's
OF MAINE

NOT TESTED ON
• ANIMALS •

NATURAL • WITH FLUORIDE

ACTIVATED
CHARCOAL
anticavity toothpaste

WHITENS TEETH*

GENTLY REMOVES
SURFACE STAINS

PREVENTS CAVITIES

NO
ANIMAL TESTING, SLS,
ARTIFICIAL FLAVORS,
SWEETENERS OR DYES

PEPPERMINT

4.0 OZ (113 g)